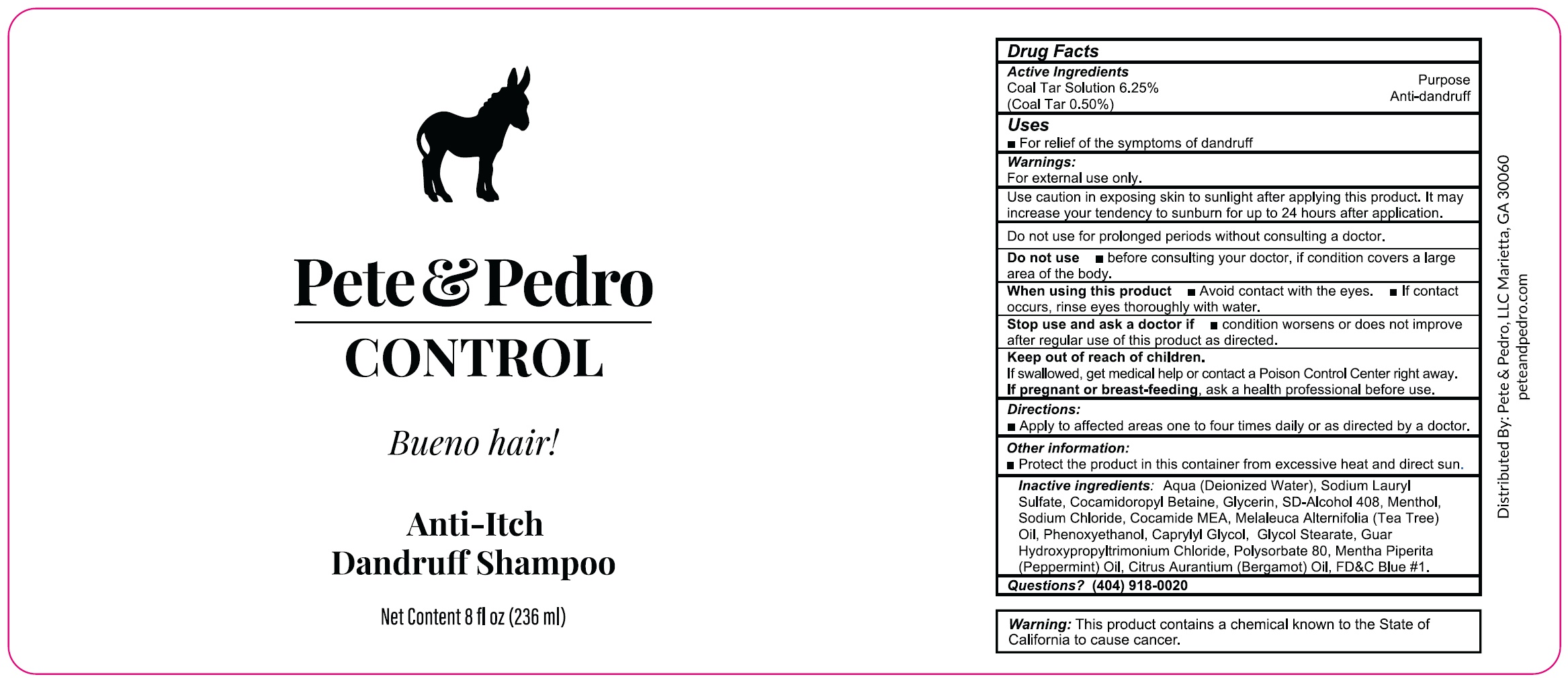 DRUG LABEL: Pete and Pedro Control Anti Itch Dandruff
NDC: 84503-508 | Form: SHAMPOO
Manufacturer: PETE AND PEDRO LLC
Category: otc | Type: HUMAN OTC DRUG LABEL
Date: 20240702

ACTIVE INGREDIENTS: COAL TAR 62.5 mg/1 mL
INACTIVE INGREDIENTS: WATER; SODIUM LAURYL SULFATE; COCAMIDOPROPYL BETAINE; GLYCERIN; MENTHOL; SODIUM CHLORIDE; COCO MONOETHANOLAMIDE; MELALEUCA ALTERNIFOLIA LEAF; PHENOXYETHANOL; CAPRYLYL GLYCOL; GLYCOL STEARATE; GUAR HYDROXYPROPYLTRIMONIUM CHLORIDE; POLYSORBATE 80; PEPPERMINT OIL; BERGAMOT OIL; FD&C BLUE NO. 1

Pete & Pedro Control Anti-Itch Dandruff Shampoo

Active Ingredients

Coal Tar Solution 6.25% (Coal Tar 0.50%)

Purpose

Anti-dandruff

Uses

- For relief of the symptoms of dandruff

Warnings:

For external use only.

Use caution in exposing skin to sunlight after applying this product. It may increase your tendency to sunburn for upto 24 hours after application.

Do not use for prolonged periods without consulting doctor.

Do not use

- before consulting your doctor, if condition covers a large area of the body.

When using this product

- Avoid contact with the eyes.
- If contact occurs, rinse eyes thoroughly with water.

Stop use and ask a doctor if

- condition worsens or does not improve after regular use of this product as directed.

Keep out of reach of children.

If swallowed, get medical help or contact a Poison Control Center right away.

If pregnant or breast-feeding,

ask a health professional before use.

Directions:

- Apply to affected areas one to four times daily or as directed by a doctor.

Other information:

- Protect the product in this container from excessive heat and direct sun.

Inactive ingredients:

Aqua (Deionized Water), Sodium Lauryl Sulfate, Cocamidopropyl Betaine, Glycerin, SD-Alcohol 408, Menthol, Sodium Chloride, Cocamide MEA, Melaleuca Alternifolia (Tea Tree) Oil, Phenoxyethanol, Caprylyl Glycol, Glycol stearate, Guar Hydroxypropyltrimonium Chloride, Polysorbate 80, Mentha Piperita (Peppermint) Oil, Citrus Aurantium (Bergamot) Oil, FD&C Blue #1.

Questions?

(404) 918-0020